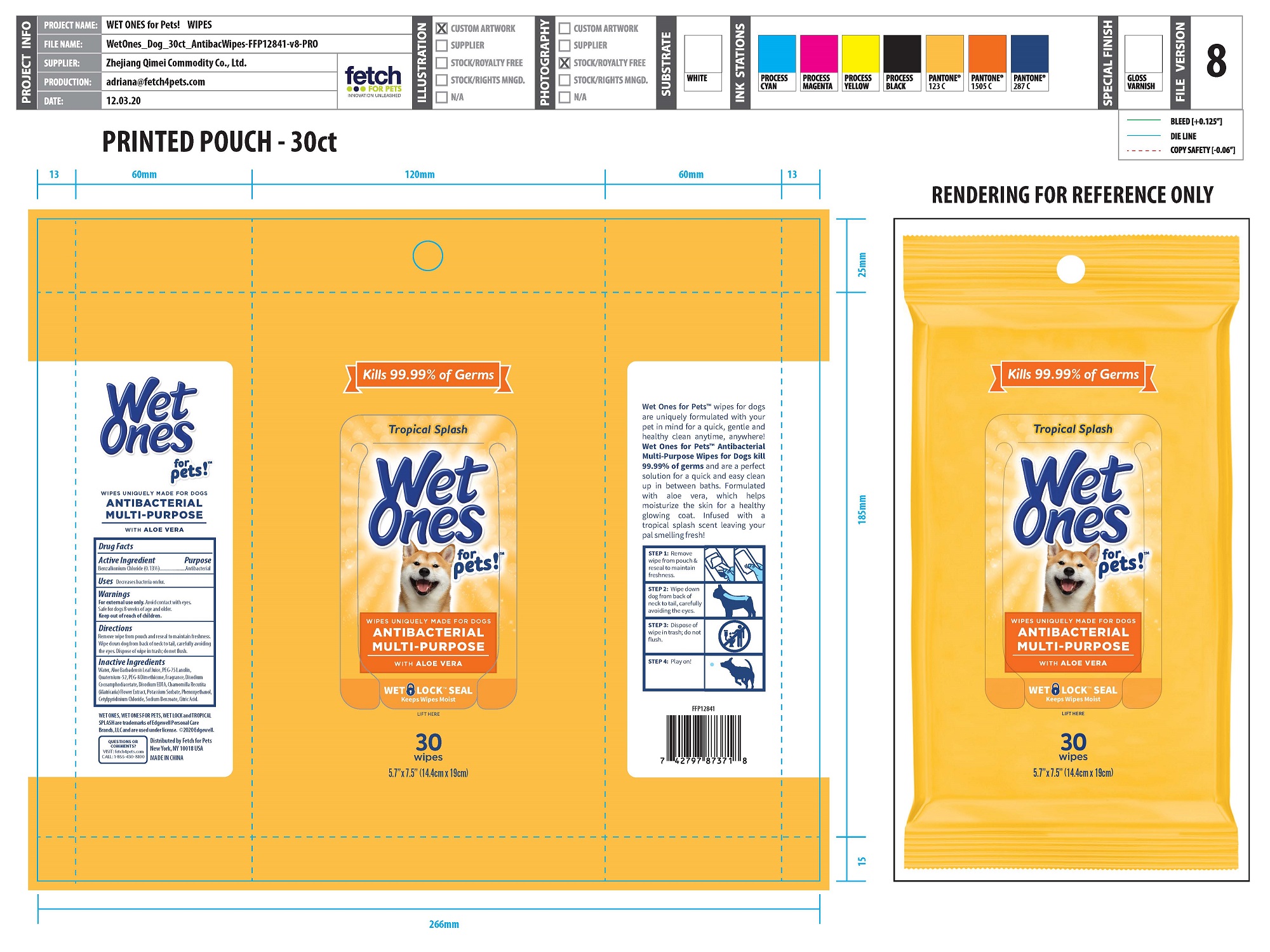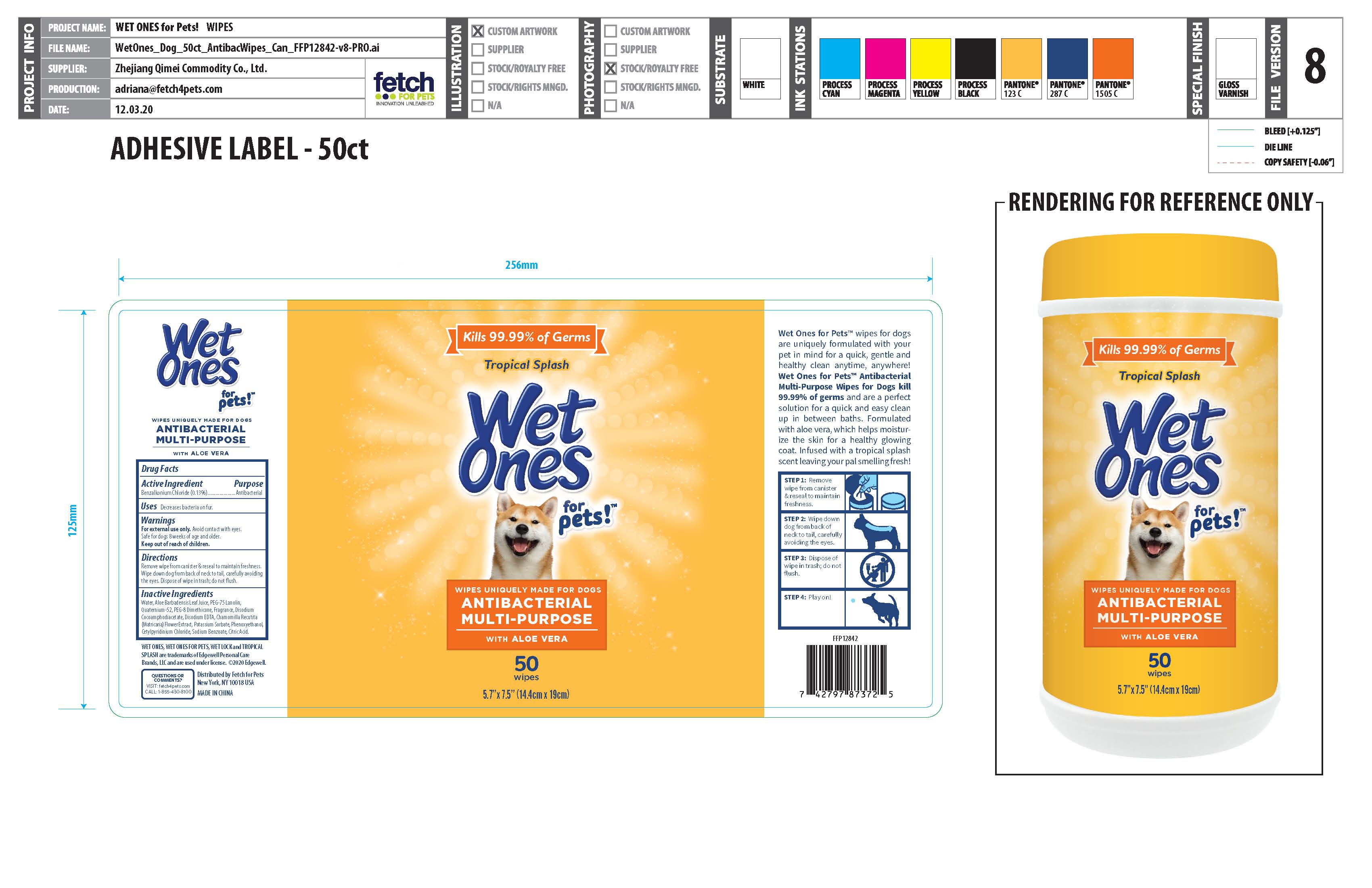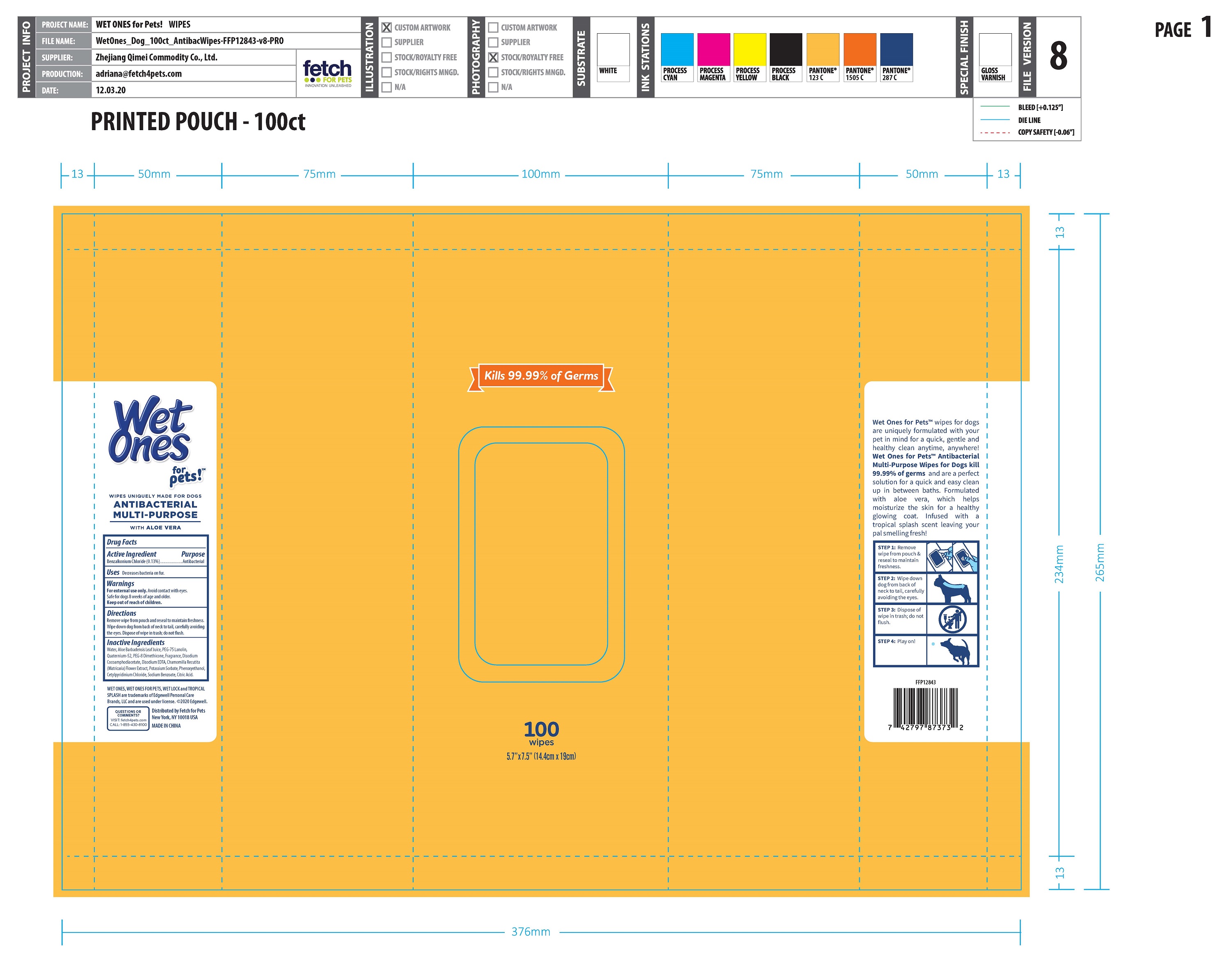 DRUG LABEL: Anti-bacterial all purpose wipe
NDC: 77720-024 | Form: CLOTH
Manufacturer: Skaffles Group Limited Liability Company
Category: animal | Type: OTC ANIMAL DRUG LABEL
Date: 20210122

ACTIVE INGREDIENTS: BENZALKONIUM CHLORIDE 0.13 g/100 g
INACTIVE INGREDIENTS: WATER; PEG-75 LANOLIN; QUATERNIUM-52; ALOE VERA LEAF; PEG-8 DIMETHICONE; DISODIUM COCOAMPHODIACETATE; DISODIUM EDTA-COPPER; CHAMOMILE; PHENOXYETHANOL; POTASSIUM SORBATE; CETYLPYRIDINIUM CHLORIDE; SODIUM BENZOATE; CITRIC ACID ACETATE

Active Ingredient

Benzalkonium Chloride 0.13%

Purpose

Antibacterial

USE

Decreases Bacteria on pets body.

Warning

For external use only.

Avoid Contact with eyes. Safe for dogs 8 weeks of age and older.

Keep out of reach of children.

Directions

Remove wipe form canister&reseal to maintian freshness.

wipe donw dog from back of neck to tail ,carefullly avoiding the eyes.

didpose of wipe in trash ,do not flush

Inactive ingredients

water,Aloe BarbadensisLeaf Juice, PEG-75 Lan olin,
Quaternium-52, PEG-8 Dim ethicone, Fragran ce, DisodiumCocoamph odiacet ate, Disodium EDTA,Cham omilla Recutita(hMatricaria) FowerExtrad,Potassium Sorbate, Phenoxyeth an olCetylpyridinium Chloride, Sodium Benzoate, CitricAcid.